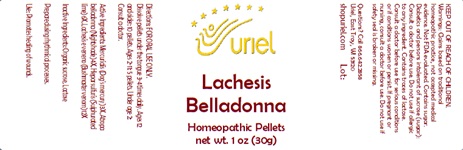 DRUG LABEL: Lachesis Belladonna
NDC: 48951-6014 | Form: PELLET
Manufacturer: Uriel Pharmacy Inc.
Category: homeopathic | Type: HUMAN OTC DRUG LABEL
Date: 20241210

ACTIVE INGREDIENTS: MERCURIALIS PERENNIS 3 [hp_X]/1 1; ATROPA BELLADONNA 4 [hp_X]/1 1; CALCIUM SULFIDE 6 [hp_X]/1 1; LACHESIS MUTA VENOM 12 [hp_X]/1 1
INACTIVE INGREDIENTS: LACTOSE; SUCROSE

Lachesis Belladonna

INDICATIONS AND USAGE

Directions: FOR ORAL USE ONLY.

DOSAGE AND ADMINISTRATION

Dissolve pellets under the tongue 3-4 times daily. Ages 12 and older: 10 pellets. Ages 2-11: 5 pellets. Under age 2: Consult a doctor.

ACTIVE INGREDIENT

Active Ingredients: Mercurialis (Dog's mercury) 3X, Atropa belladonna (Nightshade) 4X, Hepar sulfuris (Sulphurated lime) 6X, Lachesis e veneno (Bushmaster venom) 12X

Inactive Ingredient: Organic sucrose, Lactose

Prepared using rhythmical processes.

PURPOSE

Use: Promotes healing of wounds.

KEEP OUT OF REACH OF CHILDREN.

WARNINGS

Warnings: Claims based on traditional homeopathic practice, not accepted medical evidence. Not FDA evaluated. Contains sugar. Diabetics and persons intolerant of sucrose (sugar): Consult a doctor before use. Do not use if allergic to any ingredient. Contains traces of lactose. Consult a doctor before use for serious conditions or if conditions worsen or persist. If pregnant or nursing, consult a doctor before use. Do not use if safety seal is broken or missing.

QUESTIONS

Questions? Call 866.642.2858 Uriel, East Troy, WI 53120 shopuriel.com Lot: